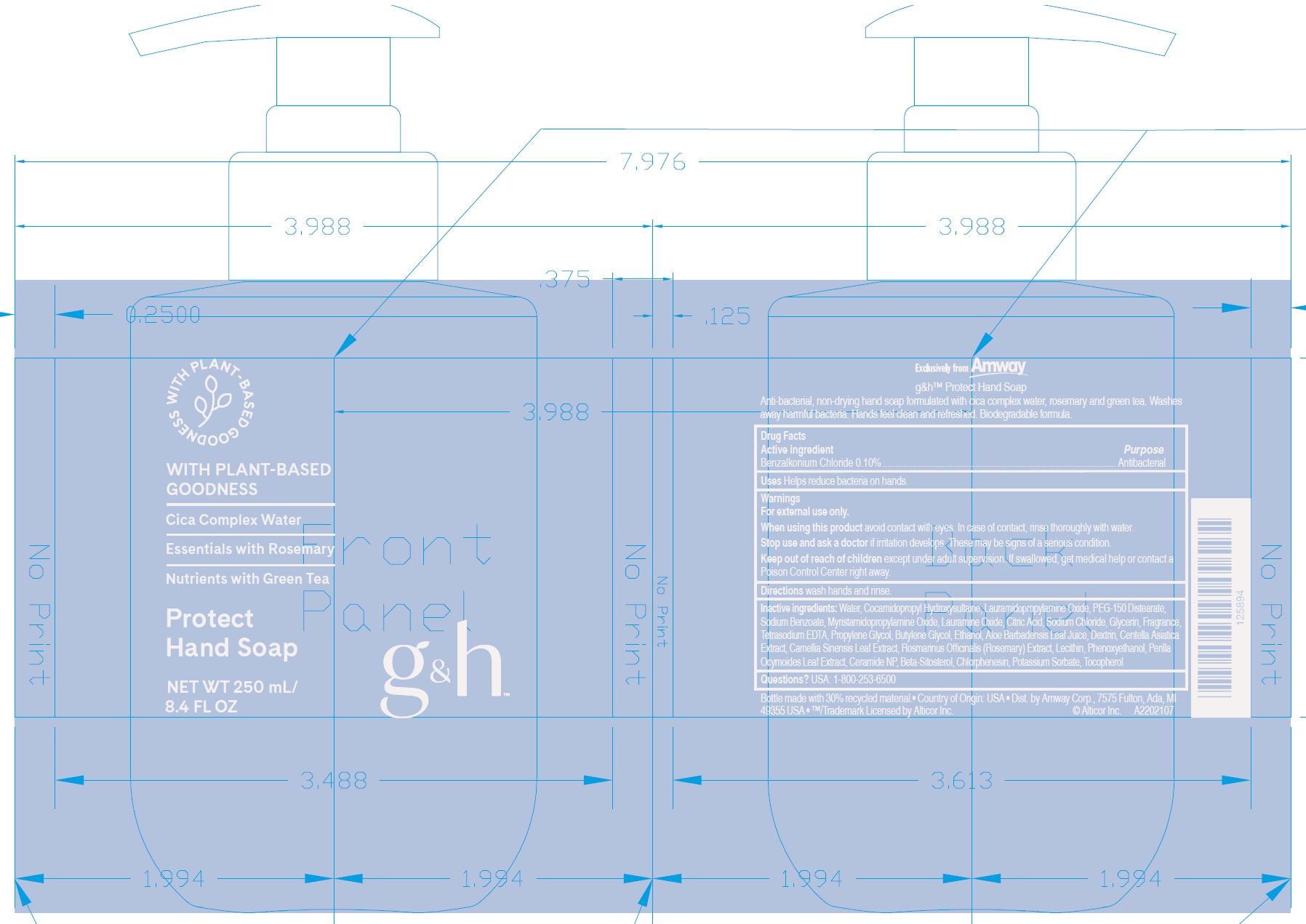 DRUG LABEL: g and h Protect Hand
NDC: 10056-026 | Form: SOAP
Manufacturer: Access Business Group LLC
Category: otc | Type: HUMAN OTC DRUG LABEL
Date: 20231023

ACTIVE INGREDIENTS: BENZALKONIUM CHLORIDE 1 mg/1 mL
INACTIVE INGREDIENTS: WATER; COCAMIDOPROPYL HYDROXYSULTAINE; LAURAMIDOPROPYLAMINE OXIDE; PEG-150 DISTEARATE; SODIUM BENZOATE; MYRISTAMIDOPROPYLAMINE OXIDE; LAURAMINE OXIDE; CITRIC ACID MONOHYDRATE; SODIUM CHLORIDE; GLYCERIN; EDETATE SODIUM; PROPYLENE GLYCOL; BUTYLENE GLYCOL; ALCOHOL; ALOE VERA LEAF; CENTELLA ASIATICA TRITERPENOIDS; GREEN TEA LEAF; ROSEMARY; PHENOXYETHANOL; PERILLA FRUTESCENS LEAF; CERAMIDE NP; .BETA.-SITOSTEROL; CHLORPHENESIN; POTASSIUM SORBATE; TOCOPHEROL

g&h Protect Hand Soap

Active ingredient

Benzalkonium Chloride 0.10%

Purpose

Antibacterial

Uses

Helps reduce bacteria on hands.

Warnings

For external use only.

When using this product

avoid contact with eyes. In case of contact, rinse thoroughly with water.

Stop use and ask a doctor

if irritation develops. These may be signs of a serious condition.

Keep out of reach of children

except under adult supervision. If swallowed, get medical help or contact a Poison Control Center right away.

Directions

wash hands and rinse.

Inactive ingredients:

Water, Cocamidopropyl Hydroxysultaine, Lauramidopropylamine Oxide, PEG-150 Distearate, Sodium Benzoate, Myristamidopropylamine Oxide, Lauramine Oxide, Citric Acid, Sodium Chloride, Glycerin, Fragrance, Tetrasodium EDTA, Propylene Glycol, Butylene Glycol, Ethanol, Aloe Barbadensis Leaf Juice, Dextrin, Centella Asiatica Extract, Camellia Sinensis Leaf Extract, Rosmarinus Officinalis (Rosemary) Extract, Lecithin, Phenoxyethanol, Perilla Ocymoides Leaf Extract, Ceramide NP, Beta-Sitosterol, Chlorphenesin, Potassium Sorbate, Tocopherol

Questions?

USA: 1-800-253-6500